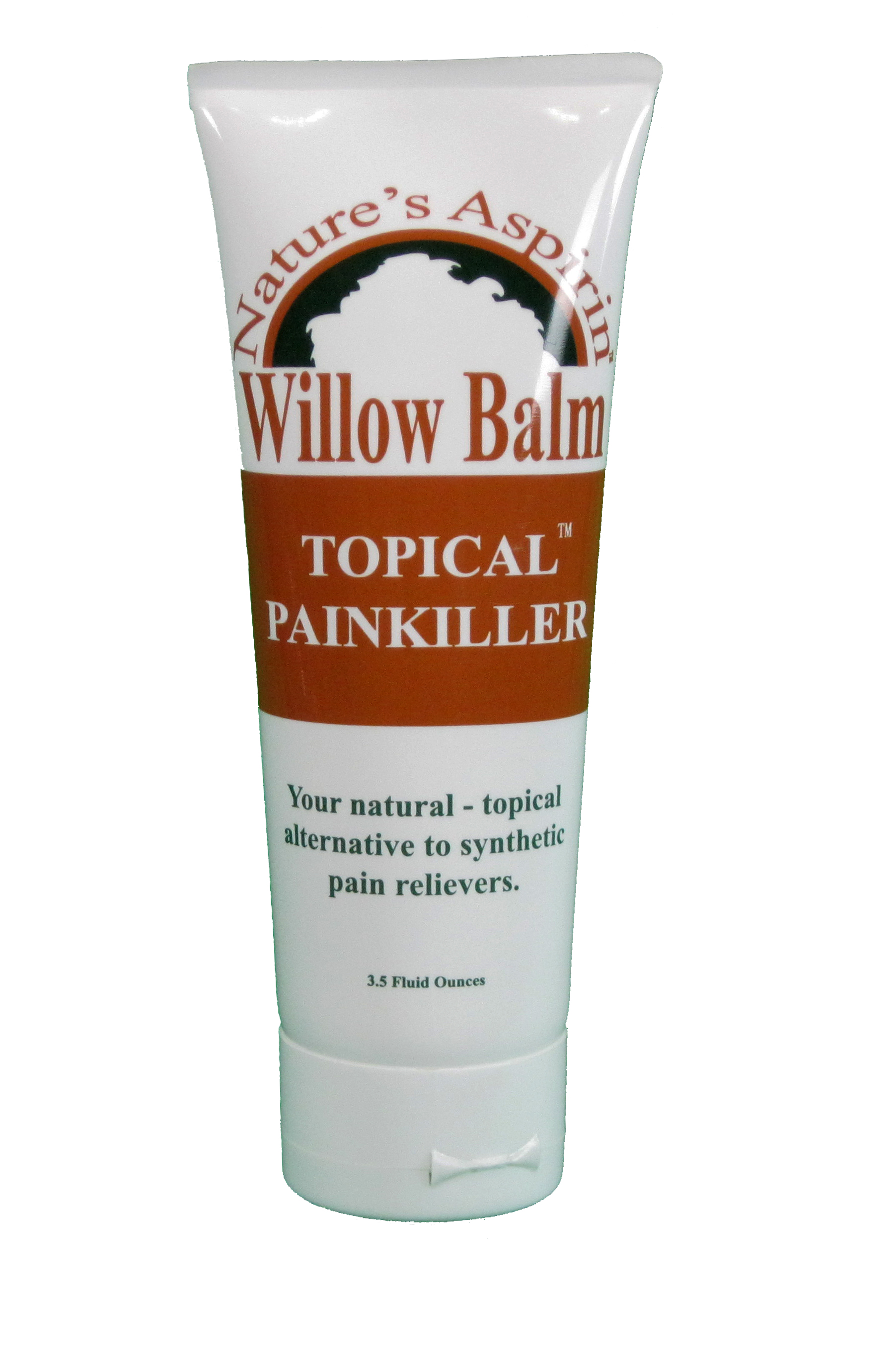 DRUG LABEL: Willow Balm
NDC: 71629-035 | Form: CREAM
Manufacturer: I Woke Up Well Distributing Inc
Category: otc | Type: HUMAN OTC DRUG LABEL
Date: 20180115

ACTIVE INGREDIENTS: MENTHOL 0.03 g/1 g
INACTIVE INGREDIENTS: PELARGONIUM GRAVEOLENS FLOWER OIL 0.013 g/1 g; LAVENDER OIL 0.013 g/1 g; PROPYLENE GLYCOL 0.095 g/1 g; WATER 0.072 g/1 g; CETYL ALCOHOL 0.0238 g/1 g; HELICHRYSUM GYMNOCEPHALUM WHOLE 0.009 g/1 g; STEARIC ACID 0.238 g/1 g; STEARYL ALCOHOL 0.119 g/1 g; ALMOND OIL 0.019 g/1 g; TROLAMINE 0.013 g/1 g; CETEARETH-10 0.476 g/1 g; SALIX ALBA BARK 0.049 g/1 g; SPEARMINT 0.002 g/1 g; EUCALYPTUS OIL 0.078 g/1 g; HYDROGENATED JOJOBA OIL/JOJOBA OIL, RANDOMIZED (IODINE VALUE 40-44) 0.0095 g/1 g; .ALPHA.,.ALPHA.-DIBROMO-D-CAMPHOR 0.078 g/1 g; ISOPROPYL PALMITATE 0.019 g/1 g; MINERAL OIL 0.571 g/1 g

Willow Balm Nature's Aspirin

Active Ingredients

Menthol 3% Counterirritant

Warnings

WARNINGS for external use only. Use only as directed. Avoid contact
with eyes and mucus membranes. Do not cover with bandage. Do not use on open wounds or damaged skin.
Keep out of reach of Children. Consult physician for children under 12.

Uses

Use for the temporary relief of minor aches and muscle pains associated with arthritis, simple backache, strains, muscle soreness and stiffness

Other Ingredients

BOTANICALS White Willow Bark, Camphor, Eucalyptus Oil, Lavender Oil, Geranium Oil, Helichrysum Gymnocephalum Oil,
Spearment Oil OTHER INGREDIENTS water, mineral oil, cetyp alcohol, stearic acid, stearyl alcohol, cetearyl alcohol,
cetereth, propylene glycol, isopropyl palmtate, almond oil, glycol monostearate, phenoxy ethanol, caprylyl glycol,
jojoba seed oil

Contact information

For more informatin contact us at: 888-609-4556, or visit www.willowbalm.com Made in the USA I Woke Up Well Distributing, Inc. US Pat. 8765194

Warnings

Keep Out Of Reach of Children

Directions

Apply the product directly to the affected area. Product may be used as necessary, but should not be used more than four times daily.

Purpose

Use for the temporary relief of minor aches and muscle pains.